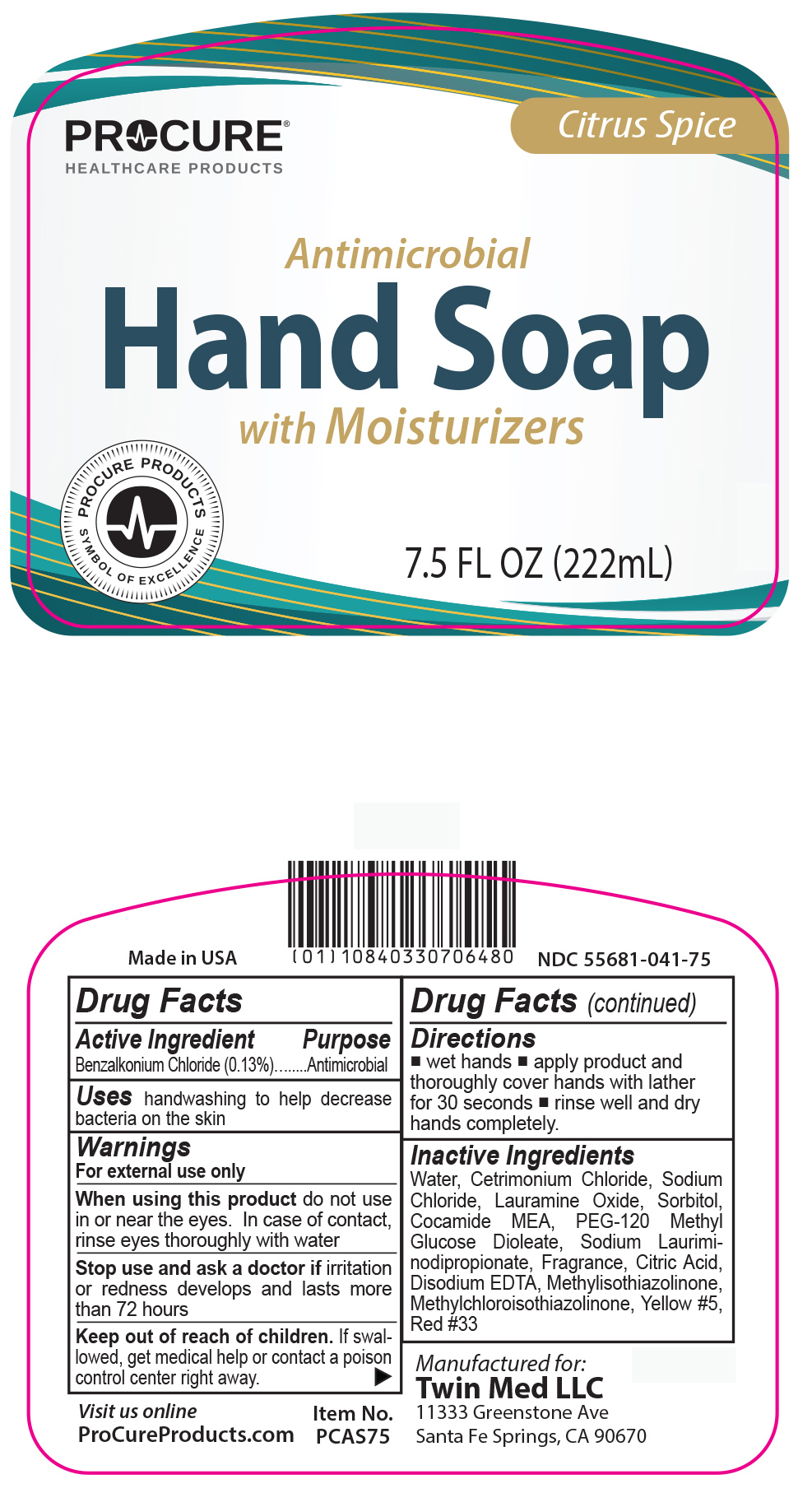 DRUG LABEL: ProCure Antimicrobial Hand
NDC: 55681-041 | Form: SOAP
Manufacturer: Twin Med LLC
Category: otc | Type: HUMAN OTC DRUG LABEL
Date: 20250904

ACTIVE INGREDIENTS: BENZALKONIUM CHLORIDE 0.13 g/100 mL
INACTIVE INGREDIENTS: EDETATE DISODIUM; FD&C YELLOW NO. 5; ANHYDROUS CITRIC ACID; PEG-120 METHYL GLUCOSE DIOLEATE; WATER; COCO MONOETHANOLAMIDE; CETRIMONIUM CHLORIDE; SODIUM CHLORIDE; LAURAMINE OXIDE; SORBITOL; SODIUM LAURIMINODIPROPIONATE; METHYLCHLOROISOTHIAZOLINONE/METHYLISOTHIAZOLINONE MIXTURE; D&C RED NO. 33

Active Ingredient

Benzalkonium Chloride (0.13%)

Purpose

Antimicrobial

Uses

Uses handwashing to help decrease bacteria on the skin

Warnings

For external use only

When using this product do not use in or near the eyes. In case of contact, rinse eyes thoroughly with water

Stop use and ask a doctor if irritation or redness develops and lasts more than 72 hours

Keep out of reach of children. If swallowed, get medical help or contact a poison control center right away

Directions

- wet hands
- apply product and thoroughly cover hands with lather for 30 seconds
- rinse well and dry hands completely

Inactive Ingredients

Inactive Ingredients Water, Cetrimonium Chloride, Sodium Chloride, Lauramine Oxide, Sorbitol, Cocamide MEA, PEG-120 Methyl Glucose Dioleate, Sodium Lauriminodipropionate, Fragrance, Citric Acid, Disodium EDTA, Methylisothiazolinone, Methylchloroisothiazolinone, Yellow #5, Red #33